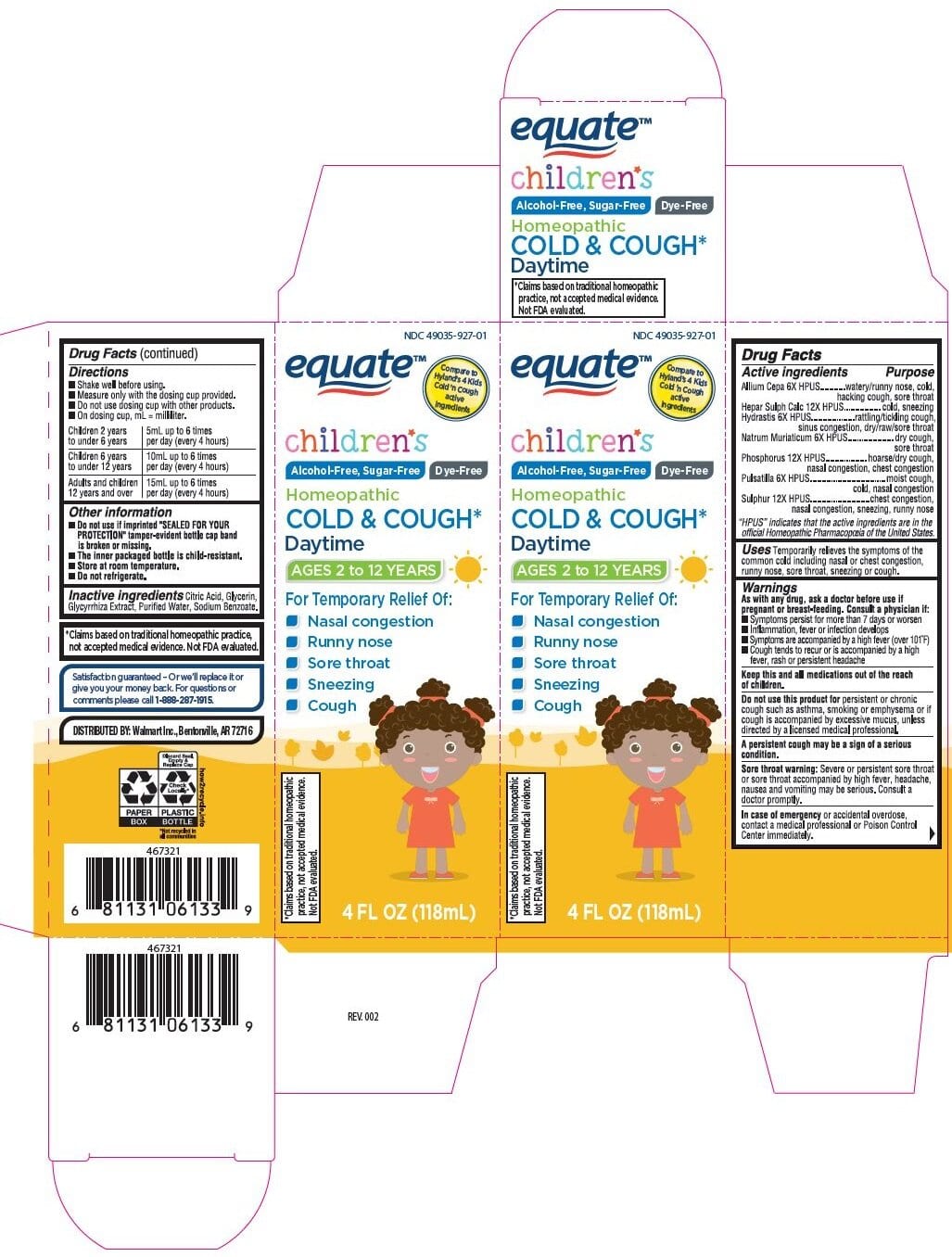 DRUG LABEL: Cold and Cough
NDC: 49035-927 | Form: LIQUID
Manufacturer:  Wal-Mart Stores, Inc. 
Category: homeopathic | Type: HUMAN OTC DRUG LABEL
Date: 20221215

ACTIVE INGREDIENTS: ONION 6 [hp_X]/1 mL; CALCIUM SULFIDE 12 [hp_X]/1 mL; PHOSPHORUS 12 [hp_X]/1 mL; ANEMONE PULSATILLA 6 [hp_X]/1 mL; SULFUR 12 [hp_X]/1 mL; SODIUM CHLORIDE 6 [hp_X]/1 mL; GOLDENSEAL 6 [hp_X]/1 mL
INACTIVE INGREDIENTS: GLYCYRRHIZA GLABRA; CITRIC ACID MONOHYDRATE; WATER; SODIUM BENZOATE; GLYCERIN

Equate Children's Cold & Cough Daytime

Drug Facts

Active Ingredients

Active ingredients | Purpose
Allium Cepa 6X HPUS | watery/runny nose, cold, hacking cough, painful throat
Hepar Sulph Calc 12X HPUS | cold, sneezing
Hydrastis 6X HPUS | rattling/tickling cough, sinus congestion, dry/raw/sore throat
Natrum Muriaticum 6X HPUS | dry cough, sore throat
Phosphorus 12X HPUS | hoarse/dry cough, nasal congestion, chest congestion
Pulsatilla 6X HPUS | moist cough, cold, nasal congestion
Sulphur 12X HPUS | chest congestion, nasal congestion, sneezing, runny nose

"HPUS” indicates that the active ingredients are in the official Homeopathic Pharmacopœia of the United States.

Uses

Temporarily relieves the symptoms of the common cold including nasal and chest congestion, runny nose, sore throat, sneezing and cough.

Warnings

As with any drug, ask a doctor before use if pregnant or breast-feeding. Consult a physician if:

- Symptoms persist for more than 7 days or worsen
- Inflammation, fever or infection develops
- Symptoms are accompanied by a high fever (over 101°F)
- Cough tends to recur or is accompanied by a high fever, rash or persistent headache

KEEP OUT OF REACH OF CHILDREN

Keep this and all medications out of the reach of children.

Do not use this product for persistent or chronic cough such as asthma, smoking or emphysema or if cough is accompanied by excessive mucus, unless directed by a licensed medical professional.

A persistent cough may be a sign of a serious condition.

Sore throat warning: Severe or persistent sore throat or sore throat accompanied by high fever, headache,nausea and vomiting may be serious. Consult a doctor promptly.

In case of emergency or accidental overdose, contact a medical professional or Poison Control Center immediately.

Drug Facts (continued)

Directions

- Shake well before using.
- Measure only with the dosing cup provided.
- Do not use dosing cup with other products.
- On dosing cup, mL = milliliter.

Children 2 years to under 6 years | 5 mL up to 6 times per day (every 4 hours)
Children 6 years to under 12 years | 10 mL up to 6 times per day (every 4 hours)
Adults and children 12 years and over | 15 mL up to 6 times per day (every 4 hours)

Other information

- Do not use if imprinted "SEALED FOR YOUR PROTECTION" tamper-evident bottle cap band is broken or missing.
- The inner packaged bottle is child-resistant.
- Store at room temperature.
- Do not refrigerate.

Inactive ingredients

Citric Acid, Glycerine, Glycyrrhiza Extract, Purified Water, Sodium Benzoate.

*Claims based on traditional homeopathic practice, not accepted medical evidence. Not FDA evaluated.

Dosage and Administration

 Directions

Shake well before using.

Measure only with the dosing cup provided.

Do not use dosing cup with other products.

On dosing cup, mL = milliliter.

removed Teaspoon

Principal Display Panel - 4 FL OZ (118 mL) Bottle Carton

NDC 49035-927-01

Equate™

Compare to

Hyland’s 4 Kids

Cold ’n Cough

active

ingredients

Children's

Alcohol Free, Sugar Free, Dye Free

Homeopathic

Cold & Cough*

Daytime

AGES 2 to 12 YEARS

For Temporary Relief of:

- Nasal Congestion

- Runny Nose

- Sore Throat

- Sneezing

- Cough

*Claims based on traditional

homeopathic practice, not

accepted medical evidence.

Not FDA evaluated.

4 FL OZ (118 mL)